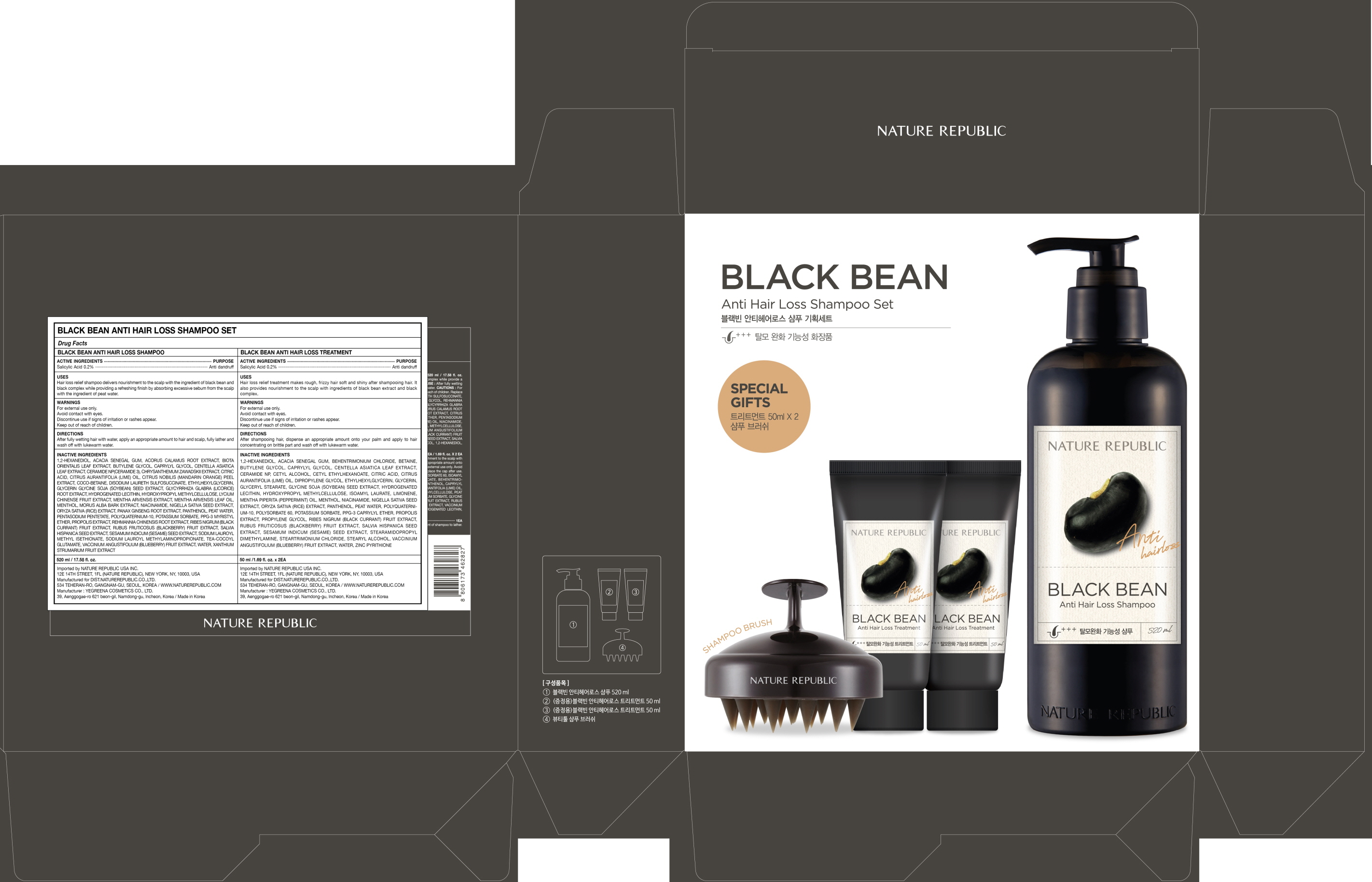 DRUG LABEL: BLACK BEAN ANTI HAIR LOSS SHAM POO SET
NDC: 51346-535 | Form: KIT | Route: TOPICAL
Manufacturer: NATURE REPUBLIC CO., LTD.
Category: otc | Type: HUMAN OTC DRUG LABEL
Date: 20201029

ACTIVE INGREDIENTS: Salicylic Acid 1.04 g/520 mL; Salicylic Acid 0.1 g/50 mL
INACTIVE INGREDIENTS: 1,2-Hexanediol; ACACIA; 1,2-Hexanediol; ACACIA

ACTIVE INGREDIENT

Salicylic Acid 0.2%

INACTIVE INGREDIENT

[BLACK BEAN ANTI HAIR LOSS SHAMPOO]

Inactive ingredients
1,2-Hexanediol, Acacia Senegal Gum, Acorus Calamus Root Extract, Biota Orientalis Leaf Extract, Butylene Glycol, Caprylyl Glycol, Centella Asiatica Leaf Extract, Ceramide NP(Ceramide 3), Chrysanthemum Zawadskii Extract, Citric acid, Citrus Aurantifolia (Lime) Oil, Citrus Nobilis (Mandarin Orange) Peel Extract, Coco-Betaine, Disodium Laureth Sulfosuccinate, Ethylhexylglycerin, Glycerin Glycine Soja (Soybean) Seed Extract, Glycyrrhiza Glabra (Licorice) Root Extract, Hydrogenated Lecithin, Hydroxypropyl Methylcellulose, Lycium Chinense Fruit Extract, Mentha Arvensis Extract, Mentha Arvensis Leaf Oil, Menthol, Morus Alba Bark Extract, Niacinamide, Nigella Sativa Seed Extract, Oryza Sativa (Rice) Extract, Panax Ginseng Root Extract, Panthenol, Peat water, Pentasodium Pentetate, Polyquaternium-10, Potassium sorbate, PPG-3 Myristyl Ether, Propolis Extract, Rehmannia Chinensis Root Extract, Ribes Nigrum (Black Currant) Fruit Extract, Rubus Fruticosus (Blackberry) Fruit Extract, Salvia Hispanica Seed Extract, Sesamum Indicum (Sesame) Seed Extract, Sodium Lauroyl Methyl Isethionate, Sodium Lauroyl Methylaminopropionate, TEA-Cocoyl Glutamate, Vaccinium Angustifolium (Blueberry) Fruit Extract, Water, Xanthium Strumarium Fruit Extract

[BLACK BEAN ANTI HAIR LOSS TREATMENT]

Inactive ingredients
1,2-Hexanediol, Acacia Senegal Gum, Behentrimonium Chloride, Betaine, Butylene Glycol, Caprylyl Glycol, Centella Asiatica Leaf Extract, Ceramide NP, Cetyl Alcohol, Cetyl Ethylhexanoate, Citric Acid, Citrus Aurantifolia (Lime) Oil, Dipropylene Glycol, Ethylhexylglycerin, Glycerin, Glyceryl Stearate, Glycine Soja (Soybean) Seed Extract, Hydrogenated Lecithin, Hydroxypropyl Methylcellulose, Isoamyl Laurate, Limonene, Mentha Piperita (Peppermint) Oil, Menthol, Niacinamide, Nigella Sativa Seed Extract, Oryza Sativa (Rice) Extract, Panthenol, Peat water, Polyquaternium-10, Polysorbate 60, Potassium Sorbate, PPG-3 Caprylyl Ether, Propolis Extract, Propylene Glycol, Ribes Nigrum (Black Currant) Fruit Extract, Rubus Fruticosus (Blackberry) Fruit Extract, Salvia Hispanica Seed Extract, Sesamum Indicum (Sesame) Seed Extract, Stearamidopropyl Dimethylamine, Steartrimonium Chloride, Stearyl Alcohol, Vaccinium Angustifolium (Blueberry) Fruit Extract, Water, Zinc Pyrithione

PURPOSE

Anti dandruff

WARNINGS

For external use only.
Avoid contact with eyes.
Discontinue use if signs of irritation or rashes appear.
Keep out of reach of children.

KEEP OUT OF REACH OF CHILDREN

Uses

[BLACK BEAN ANTI HAIR LOSS SHAMPOO]

Uses
Hair loss relief shampoo delivers nourishment to the scalp with the ingredient of black bean and black complex while providing a refreshing finish by absorbing excessive sebum from the scalp with the ingredient of peat water.

[BLACK BEAN ANTI HAIR LOSS TREATMENT]

Uses
Hair loss relief treatment makes rough, frizzy hair soft and shiny after shampooing hair. It also provides nourishment to the scalp with ingredients of black bean extract and black complex.

Directions

[BLACK BEAN ANTI HAIR LOSS SHAMPOO]

Directions
After fully wetting hair with water, apply an appropriate amount to hair and scalp, fully lather and wash off with lukewarm water.

[BLACK BEAN ANTI HAIR LOSS TREATMENT]

Directions
After shampooing hair, dispense an appropriate amount onto your palm and apply to hair concentrating on brittle part and wash off with lukewarm water.